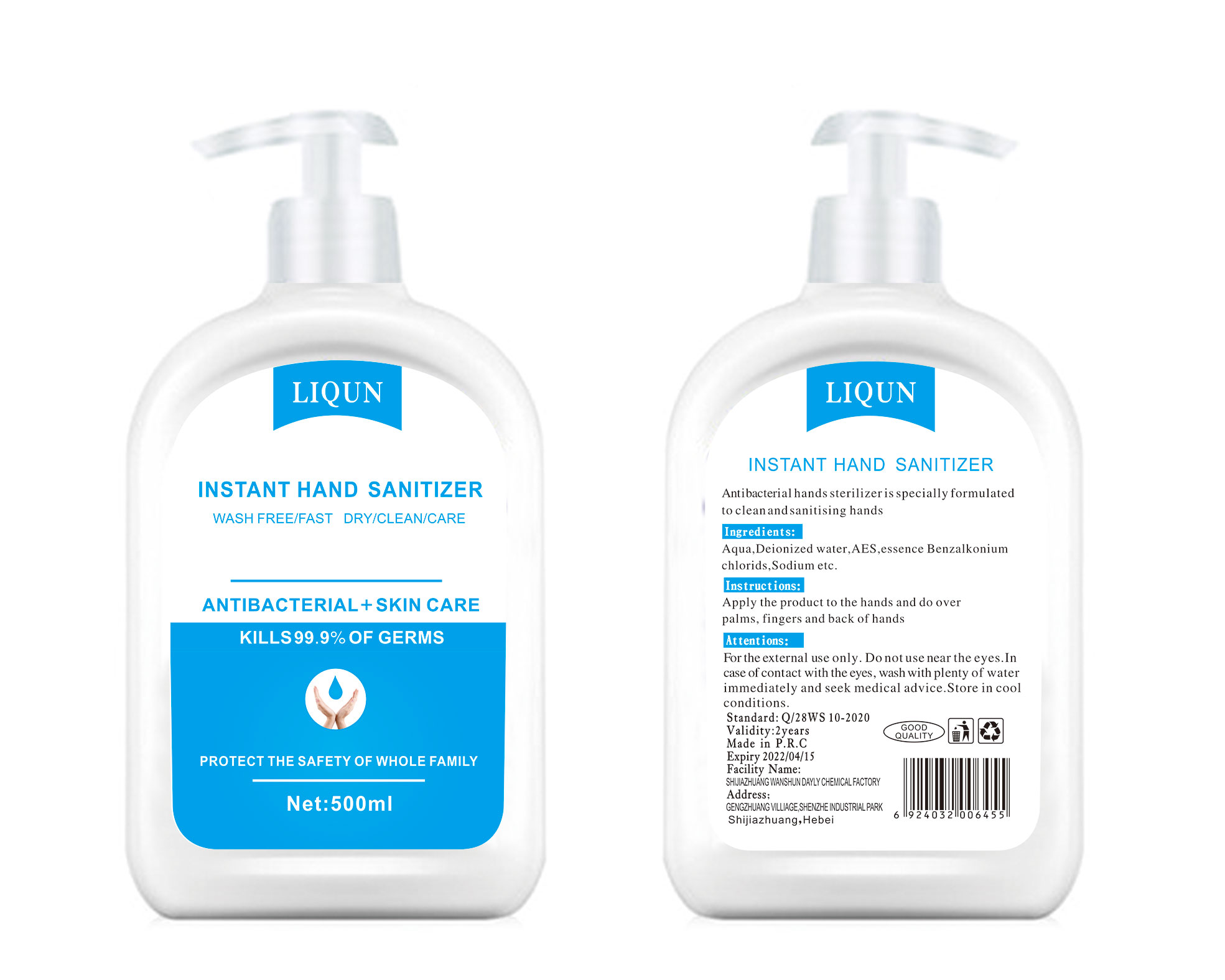 DRUG LABEL: INSTANT HAND SANITIZER
NDC: 78421-1001 | Form: LIQUID
Manufacturer: Shijiazhuang Wanshun Dayly Chemical Factory
Category: otc | Type: HUMAN OTC DRUG LABEL
Date: 20200601

ACTIVE INGREDIENTS: BENZALKONIUM CHLORIDE 3 g/500 mL
INACTIVE INGREDIENTS: WATER; PROPYLENE GLYCOL; .ALPHA.-TOCOPHEROL, DL-; SODIUM LAURETH-5 SULFATE

Wanshun, Hand Sanitizer, 500mL

Active Ingredient(s)

Benzalkonium chloride 6mg/mL. Purpose: Antimicrobial

Purpose

Antimicrobial.

Use

Antibacterial, hands sterilizer, is specially formulated to clean and sanitising hands.

Warnings

For the external use only.

Do not use near the eyes.

In case of contact with the eyes, wash with plenty of water immediately and seek medical advice.

WHEN USING

When using: avoid direct contact with eyes and damaged skin; if it gets in your eyes accidentally, please rinse with water.

Stop use and ask a doctor if irritation or rash occurs. These may be signs of a serious condition.

Keep out of reach of children.

Directions

Apply the product to the hands and do over palms, fingers, and back of hands.

Other information

Storage in cool conditions.

Inactive ingredients

Deionized water (Aqua), AES, Propylene glycol, Vitamin E.